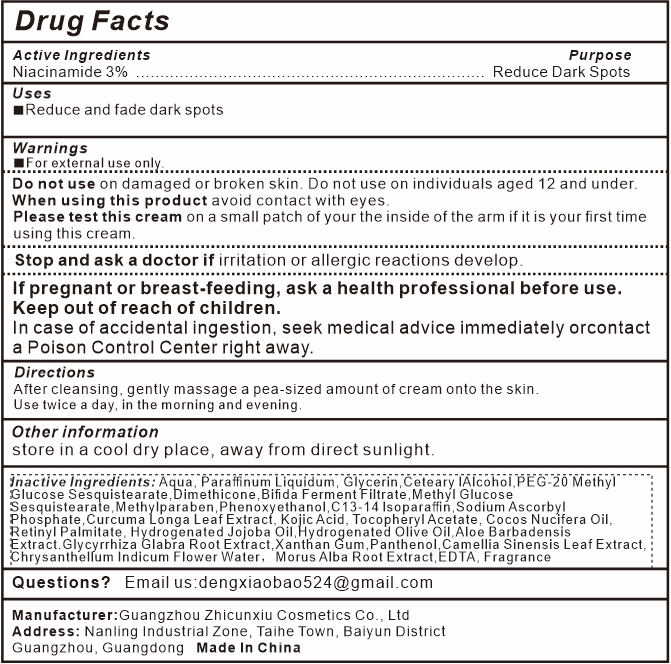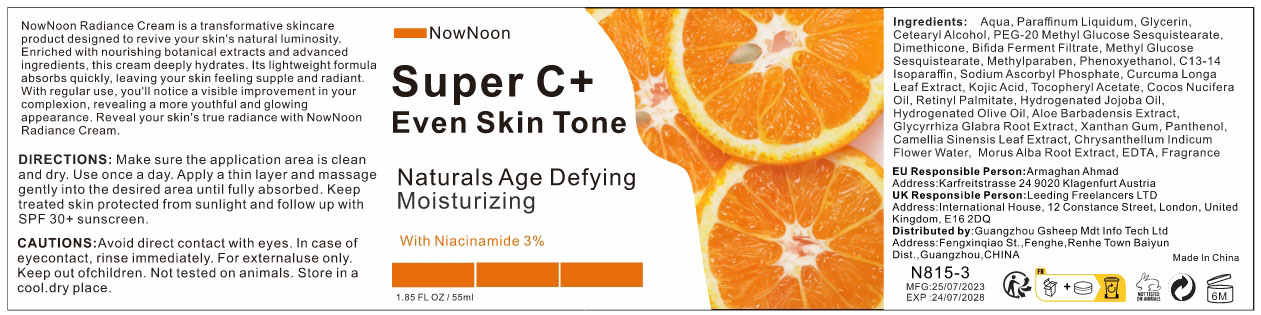 DRUG LABEL: NowNoon Super C Even Skin Tone Cream
NDC: 84037-0005 | Form: CREAM
Manufacturer: Guangzhou Zhicunxiu Cosmetics Co., Ltd
Category: otc | Type: HUMAN OTC DRUG LABEL
Date: 20240429

ACTIVE INGREDIENTS: NIACINAMIDE 30 mg/1 mL
INACTIVE INGREDIENTS: CETYL ALCOHOL; DIMETHICONE; PEG-20 METHYL GLUCOSE SESQUISTEARATE; GLYCERIN; WATER; METHYLPARABEN; PHENOXYETHANOL; C13-14 ISOPARAFFIN; METHYL GLUCOSE SESQUISTEARATE; MINERAL OIL

NowNoon Super C+ Even Skin Tone Cream

Active Ingredient

Niacinamide 3%

Purpose

Reduce Dark Spots

Uses

Reduce and fade dark spots

Warnings

For external use only

Do not use ondamaged or broken skin. Do not use on individuals aged 12 and under .

When using this productavoid contact with eyes.

Please test this cream on a small patch of your dark spot if it is your first time using this cream.
Stop and ask a doctor if irritation or allergic reactions develop.
If pregnant or breast-feeding,ask a health professional before use.

Keep out of reach of children.

In case of accidental ingestion, seek medical advice immediately or
contact a Poison Control Center right away.

Directions

After cleansing, gently massage a pea-sized amount of cream onto the skin, focusing on the blotchy areas and dark spots.

Use twice a day, in the morning and evening.

Other Information

store in a cool dry place, away from direct sunlight.

Inactive ingredients

Aqua, Paraffinum Liquidum, Glycerin,Ceteary lAlcohol,PEG-20 Methyl Glucose Sesquistearate,Dimethicone,Bifida Ferment Filtrate,Methyl Glucose Sesquistearate,Methylparaben,Phenoxyethanol,C13-14 lsoparaffin,Sodium Ascorbyl Phosphate,Curcuma Longa Leaf Extract, Kojic Acid, Tocopheryl Acetate, Cocos Nucifera Oil, Retinyl Palmitate, Hydrogenated Jojoba Oil,Hydrogenated Olive Oil,Aloe Barbadensis Extract.Glycyrrhiza Glabra Root Extract,Xanthan Gum,Panthenol,Camellia Sinensis Leaf Extract, Chrysanthellum Indicum Flower Water，Morus Alba Root Extract,EDTA, Fragrance

Questions?

Email us at dengxiaobao524@gmail.com